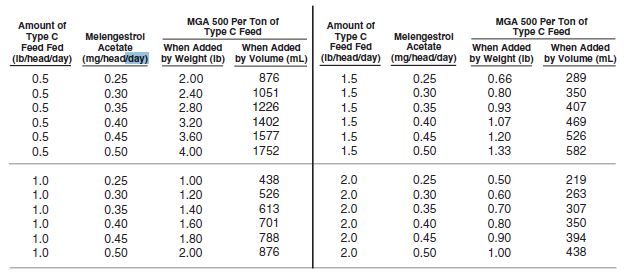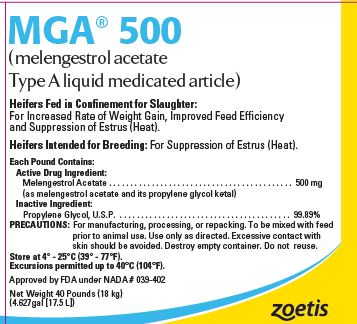 DRUG LABEL: MGA
NDC: 54771-1547 | Form: LIQUID
Manufacturer: Zoetis Inc.
Category: animal | Type: OTC ANIMAL DRUG LABEL
Date: 20230206

ACTIVE INGREDIENTS: MELENGESTROL ACETATE 500 mg/.45 kg

MGA® 500

MGA® 500

(melengestrol acetate Type A liquid medicated article)

Heifers Fed in Confinement for Slaughter:
For Increased Rate of Weight Gain, Improved Feed Efficiency and Suppression of Estrus (Heat).
Heifers Intended for Breeding: For Suppression of Estrus (Heat).

Each Pound Contains:

Active Drug Ingredient:

Melengestrol Acetate . . . . . . . . . . . . . . . . . . . . . . . . . . . . . . . . . . . . . . . . . . . 500 mg

(as melengestrol acetate and its propylene glycol ketal)

Inactive Ingredient:

Propylene Glycol, U.S.P. . . . . . . . . . . . . . . . . . . . . . . . . . . . . . . . . . . . . . . . . 99.89%

PRECAUTIONS: For manufacturing, processing, or repacking. To be mixed with feed prior to animal use. Use only as directed. Excessive contact with skin should be avoided. Destroy empty container. Do not reuse.

Store at 4° - 25°C (39° - 77°F).

Excursions permitted up to 40°C (104°F).

Approved by FDA under NADA # 039-402

Net Weight 40 Pounds (18 kg)

(4.627gal [17.5 L])

DIRECTIONS FOR USE

Heifers Fed in Confinement for Slaughter:

MGA 500 (melengestrol acetate Type A liquid medicated article) should be thoroughly mixed in liquid Type C medicated feed which must be fed at 0.5 to 2.0 pounds per head daily to provide 0.25 to 0.5 mg of melengestrol acetate per head per day. Average daily intakes approximating the middle of this range provide the most optimal and economical improvements in rate of gain and feed utilization. Constant daily intakes of 0.35 to 0.50 mg per head per day give a high degree of estrus suppression. Levels of 0.25 to 0.35 mg provide a lower but still effective degree of estrus suppression.

Heifers Intended for Breeding:

MGA 500 should be thoroughly mixed in the supplement to provide 0.5 mg of melengestrol acetate per head per day.

WARNINGS: Not for human use. Restricted Drug (California)—Use Only As Directed

PRECAUTIONS: Not effective in steers and spayed heifers.

Heifers Fed in Confinement for Slaughter:

Withdrawal periods of three to five days or more should be avoided to prevent the possibility that the heifers may come into estrus (heat) at loading time.

Heifers Intended for Breeding:

Do not exceed 24 days of feeding of melengestrol acetate to heifers intended for breeding. A reduced conception rate can be expected if heifers are bred at estruses observed within 1 to 12 days after withdrawal of melengestrol acetate, whereas heifers bred at subsequent observed estruses are expected to have normal conception rates.

MIXING DIRECTIONS

Liquid Type B and C medicated feeds containing melengestrol acetate must have a pH of 4.0 to 8.0 and their labels must bear appropriate mixing directions. Mixing directions for liquid Type B or C feeds stored in recirculation tank systems are: “Recirculate immediately prior to use for no less than 10 minutes, moving not less than 1 percent of the tank contents per minute from the bottom of the tank to the top. Recirculate daily, as directed in this paragraph even when the Type B (or C) feed is not used.” Mixing directions for liquid Type B and C feeds stored in mechanical, air or other agitation-type tank systems are: “Agitate immediately prior to use for not less than 10 minutes, creating a turbulence at the bottom of the tank that is visible at the top. Agitate daily, as directed in this paragraph, even when the Type B (or C) feed is not used.”
Intermediate medicated feeds should not be made from MGA 500 except as a part of a continuous mixing operation to make a complete liquid Type B or Type C medicated feed.
Thoroughly mix 0.5 to 4 pounds of MGA 500 per ton of a non-medicated feed to prepare a Type C medicated feed containing 0.25 to 2.0 grams of melengestrol acetate per ton. The following Table may be used as a guide in determining the amount of MGA 500 to be added to prepare a ton of Type C medicated feed.

Table for dosing

Type B medicated feed containing 4 to 10 grams melengestrol acetate per ton may be manufactured by thoroughly mixing 8 to 20 lbs of MGA 500 (melengestrol acetate Type A liquid medicated article) with 1992 to 1980 lbs of non-medicated feed. Labeling for such Type B feed shall contain directions for manufacturing Type C medicated feeds containing 0.25 to 2.0 grams melengestrol acetate per ton (0.125 to 1.0 mg/lb). The Type C medicated feed, containing melengestrol acetate, must be top dressed on grain or roughage or mixed with a complete ration at the rate of 0.5 to 2.0 pounds per head per day. Good manufacturing practice regulations must be adhered to in manufacturing feeds containing MGA 500.

zoetis

Distributed by:
Zoetis Inc.
Kalamazoo, MI 49007

40029752